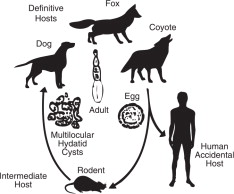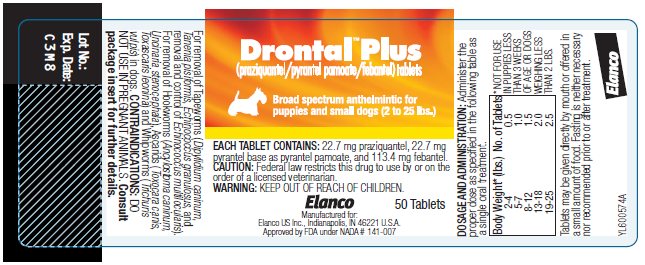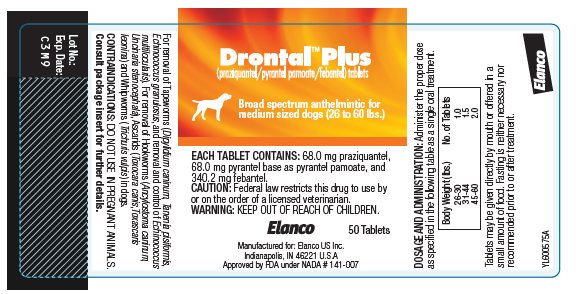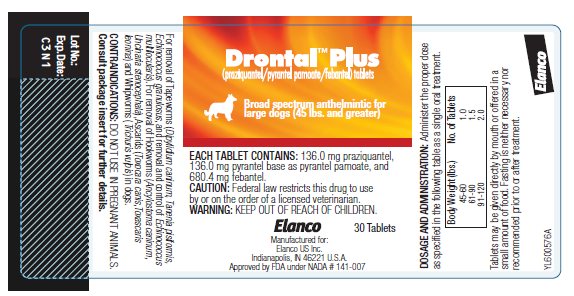 DRUG LABEL: Drontal Plus
NDC: 58198-0065 | Form: TABLET
Manufacturer: Elanco US Inc.
Category: animal | Type: PRESCRIPTION ANIMAL DRUG LABEL
Date: 20260224

ACTIVE INGREDIENTS: PRAZIQUANTEL 22.7 mg/1 1; PYRANTEL PAMOATE 22.7 mg/1 1; FEBANTEL 113.4 mg/1 1

Elanco™

Drontal™ Plus

(praziquantel/pyrantel pamoate/febantel) Tablets

Broad Spectrum Anthelmintic for Dogs

CAUTION: Federal law restricts this drug to use by or on the order of a licensed veterinarian.

DESCRIPTION:

Drontal Plus (praziquantel/pyrantel pamoate/ febantel) Broad Spectrum Anthelmintic Tablets are available in three sizes. Each size is scored for convenient oral administration.

Each Drontal Plus Tablet for Puppies and Small Dogs contains 22.7 mg praziquantel, 22.7 mg pyrantel base as pyrantel pamoate and 113.4 mg febantel.

Each Drontal Plus Tablet for Medium Sized Dogs contains 68.0 mg praziquantel, 68.0 mg pyrantel base as pyrantel pamoate and 340.2 mg febantel.

Each Drontal Plus Tablet for Large Dogs contains 136.0 mg praziquantel, 136.0 mg pyrantel base as pyrantel pamoate, and 680.4 mg febantel.

ACTION:

Drontal Plus Tablets contain three active ingredients having different modes of action and spectra of activity. Praziquantel is active against cestodes (tapeworms). Praziquantel is absorbed, metabolized in the liver and excreted in the bile. Upon entering the digestive tract from the bile, cestocidal activity is exhibited.^1 Following exposure to praziquantel, the tapeworm loses its ability to resist digestion by the mammalian host. Because of this, whole tapeworms, including the scolices, are very rarely passed after administration of praziquantel. In many instances only disintegrated and partially digested pieces of tapeworms will be seen in the stool. The majority of tapeworms are digested and are not found in the feces.

Pyrantel pamoate is active against hookworms and ascarids. Pyrantel pamoate acts on the cholinergic receptors of the nematode resulting in spastic paralysis. Peristaltic action of the intestinal tract then eliminates the parasite.^2

Febantel is active against nematode parasites including whipworms. Febantel is rapidly absorbed and metabolized in the animal. Available information suggests that the parasite's energy metabolism is blocked, leading to energy exchange breakdown and inhibited glucose uptake.

Laboratory efficacy and clinical studies conducted with Drontal Plus Tablets demonstrate that each of the three active ingredients act independently without interference. The combined tablet formulation provides a wide spectrum of activity against the indicated species of intestinal helminths.

INDICATIONS:

Drontal Plus (praziquantel/pyrantel pamoate/ febantel) Broad Spectrum Anthelmintic Tablets are indicated for removal of Tapeworms (Dipylidium caninum, Taenia pisiformis, Echinococcus granulosus, and removal and control of Echincoccus multilocularis). For removal of Hookworms (Ancylostoma caninum, Uncinaria stenocephala), Ascarids (Toxocara canis, Toxascaris leonina), and Whipworms (Trichuris vulpis) in dogs.

CONTRAINDICATIONS:

DO NOT USE IN PREGNANT ANIMALS. Dogs treated with elevated levels (6 consecutive days with 3 times the labeled dosage rate) of the combination of febantel and praziquantel in early pregnancy demonstrated an increased incidence of abortion and fetal abnormalities.^8 The effects of Drontal Plus on pregnant animals have not been determined.

There are no known contraindications against the use of praziquantel or pyrantel pamoate in dogs.

USE DIRECTIONS

DOSAGE: The presence of parasites should be confirmed by laboratory fecal examination. Weigh the animal before treatment. Administer the proper dosage as specified in the following table as a single oral treatment.

DOSAGE CHARTS
Drontal Plus Tablets for Puppies and Small Dogs* (2 - 25 lbs.) |  | Drontal Plus Tablets for Medium Sized Dogs (26 - 60 lbs.) |  | Drontal Plus Tablets for Large Dogs (45 lbs. and greater)
Body Wt. (lbs.) | No. of Tablets | Body Wt. (lbs.) | No. of Tablets | Body Wt. (lbs.) | No. of Tablets
2 – 4 | 0.5 | 26 – 30 | 1.0 | 45 – 60 | 1.0
5 – 7 | 1.0 | 31 – 44 | 1.5 | 61 – 90 | 1.5
8 – 12 | 1.5 | 45 – 60 | 2.0 | 91 – 120 | 2.0
13 – 18 | 2.0
19 – 25 | 2.5
*NOT FOR USE IN PUPPIES LESS THAN 3 WEEKS OF AGE OR DOGS WEIGHING LESS THAN 2 LBS.

ADMINISTRATION: Drontal Plus Tablets have been developed for oral administration. Tablets may be given directly by mouth or offered in a small amount of food. Fasting is neither necessary nor recommended prior to or after treatment.

RETREATMENT: For those animals living where reinfections are likely to occur, clients should be instructed in the steps to optimize prevention; otherwise, retreatment may be necessary. This is true in cases of Dipylidium caninum where reinfection is almost certain to occur if fleas are not removed from the animal and its environment. In addition, for control of Echinococcus multilocularis, a program of regular treatment every 21 to 26 days may be indicated (see E. multilocularis section below).

ECHINOCOCCUS MULTILOCULARIS: Echinococcus multilocularis is a tapeworm species usually found in wild canids, including foxes, coyotes and wolves. The parasite has also been identified in domestic dogs and cats and is potentially a serious public health concern because it may infect humans.

The life cycle of the parasite is based on a predator-prey relationship as depicted.

The adult tapeworm is small (1-4mm) and resides in the intestinal tract of the definitive host (wild or domestic canids). Eggs from the adult tapeworm are shed in the feces. Rodents such as mice and voles serve as the intermediate host. Eggs ingested by rodents develop in the liver, lungs and other organs to form multilocular cysts. The life cycle is completed after a canid consumes a rodent infected with cysts. Larvae within the cyst develop into adult tapeworms in the intestinal tract of the canid. Eggs may be passed in the feces of the canid approximately 28 days later.

This parasite poses a serious public health problem because of the possibility for human involvement in the life cycle. If eggs shed by an infected canid are accidentally ingested, a highly pathogenic condition (Alveolar Hydatid Disease) results from development of the cyst stage in humans.

The original geographic distribution of E. multilocularis was primarily confined to northern areas of North America. Current evidence indicates migration of the parasite well into the continental United States.^3,4

Domestic dogs living in E. multilocularis endemic areas that roam freely with the opportunity to catch wild rodents are at risk of infection. Pet owners should be advised on how to minimize this risk. Proper restraint of dogs should be encouraged, along with regular treatment with Drontal Plus Tablets, following the dosing schedule aforementioned and precautions indicated below.

Additional information on the life cycle and epidemiology of this parasite is available in veterinary parasitology texts.^5,6

DIAGNOSIS: Diagnosis of E. multilocularis in canids is difficult. The adult tapeworm produces no clinical signs of infection. Tapeworm segments (proglottids) are usually not observed in the feces. E. multilocularis eggs, observed using microscopic fecal examination procedures, are similar in appearance to those of common species such as Taenia pisiformis.

Assistance in the diagnosis of E. multilocularis may be available from a state veterinary diagnostic laboratory. Additional information regarding areas where E. multilocularis is suspected or has been confirmed may be obtained from area veterinary schools or the Centers for Disease Control in Atlanta, GA.

TREATMENT: Dogs infected with E. multilocularis should be treated to prevent exposure of humans to infective eggs and to break the parasite's life cycle.

The dosage of Drontal Plus Tablets for removal of E. multilocularis is the same as that indicated for the removal of the other tapeworm species listed on the label. Laboratory efficacy studies have demonstrated the recommended dosage is 100% effective.

Under condition of continual exposure to wild rodents, retreatment of the dog at 21-26 day intervals is recommended to prevent the shedding of infectious eggs.

PRECAUTIONS:

Strict hygienic precautions should be taken when handling dogs or feces suspected of harboring E. multilocularis. Infected dogs treated for the first time with Drontal Plus Tablets and dogs treated at intervals greater than 28 days may shed eggs in the feces after treatment. The animal should be held in the clinic during this interval and all feces should be incinerated or autoclaved. If these procedures are not possible, the eggs can be destroyed by soaking the feces in a sodium hypochlorite (bleach) solution of 3.75% or greater.^7 All areas where the animal was maintained or in contact with should be thoroughly cleaned with sodium hypochlorite and allowed to dry completely before reuse.

EFFICACY:

A total of 176 dogs and puppies with naturally acquired or experimental parasite infections were included in 4 well-controlled laboratory studies to establish the efficacy of Drontal Plus Tablets. In addition, 103 dogs and puppies were included in clinical field studies conducted in 5 veterinary clinics at different geographic locations throughout the United States to further evaluate safety and efficacy. These studies included dogs of various sizes, ages and breeds. Data from these studies demonstrated Drontal Plus Tablets are safe and efficacious for the removal of the parasite species indicated on the label when used as directed.

Results obtained in the laboratory and clinical studies indicate small numbers of hookworm or roundworm eggs may be passed in the feces for up to 7 days after treatment although the worms themselves were eliminated. A follow-up fecal examination should be conducted 2 to 4 weeks after treatment to determine the need for retreatment.

ADVERSE REACTIONS:

None of the 103 dogs treated with Drontal Plus Anthelmintic Tablets in the clinical field studies exhibited drug-related side effects.

CONTACT INFORMATION:

For product questions, to report adverse reactions, or for a copy of the Safety Data Sheet (SDS), call Elanco Product & Veterinary Support at 888-545-5973. For additional information about reporting adverse drug experiences for animal drugs, contact FDA at 1-888-FDA-VETS or http://www.fda.gov/reportanimalae.

ANIMAL SAFETY:

Controlled safety evaluations have been conducted in dogs with Drontal Plus (praziquantel/pyrantel pamoate/febantel) Broad Spectrum Anthelmintic Tablets. Dogs receiving up to 5 times the label dosage (35 mg praziquantel, 35 mg pyrantel pamoate and 179 mg febantel per kg of body weight) for 3 consecutive days (3 times the label duration) showed clinical signs of vomition and non-formed stools. One dog receiving a 3 times labeled dose had elevated SGPT, SGOT, CPK and GGT readings (outside of normal range) at 6 days post-treatment. No additional findings were noted in hematology/clinical chemistry parameters nor were there any treatment-related histological lesions. Vomition was the only side effect observed when dogs received a single treatment of 61 mg praziquantel, 61 mg pyrantel pamoate and 305 mg febantel/kg with one dog having an elevated SGPT reading (outside of normal range) at 24 hours post-treatment which had returned to normal by 7 days.

WARNING:

KEEP OUT OF REACH OF CHILDREN.

STORAGE CONDITIONS:

Drontal Plus Tablets should be stored at controlled room temperatures between 59-86°F (15-30°C).

HOW SUPPLIED:

Each tablet size is available in bottles of 50 (puppies and small dogs, medium sized dogs) or 30 (large dogs).

50 Tablets/Bottle | (Puppies and Small Dogs)
50 Tablets/Bottle | (Medium Sized Dogs)
30 Tablets/Bottle | (Large Dogs)

REFERENCES:

^1 Andrews P. 1976. Pharmacokinetlc Studies with DRONCIT in Animals Using a Biological Assay. Veterinary Medical Review. 2:154-165.

^2 Campbell WC. 1986. The Chemotherapy of Parasitic Infections. J. Parasit. 72(1):45-61.

^3 Hildreth MB Johnson MD and Kazacos KR. 1991. A Zoonosis of Increasing Concern in the United States. Compendium for Cont. Ed. 13(5): 727-740.

^4 Lieby PD Carney WP and Woods CE. 1970. Studies on Sylvatic Echinococcosis, III. Host Occurrence and Geographic Distribution of Echinococcus multilocularis in the North Central United States. J. Parasit. 56(6): 1141-1150.

^5 Georgi JR and Georgi ME. 1990. Parasitology for Veterinarians. W.B. Saunders Co. 118-138.

^6 Soulsby EJL. 1982. Helminths, Arthropods and Protozoa of Domesticated Animals. 7th Edition. Lea & Febiger. 118-138.

^7 Craig PS and McPharson CNL. 1988. Sodium Hypochlorite as an Ovicide for Echinococcus. Ann Trop Med. and Parasit. 82(2): 211-213.

^8 Freedom of Information Summary (FOI) NADA 133-953 Vercom Paste (febantel and praziquantel).

Elanco™

Manufactured for:
Elanco US Inc.
Indianapolis, IN 46221 U.S.A.

Approved by FDA under NADA # 141-007

Drontal, Elanco and the diagonal bar logo are trademarks of Elanco or its affiliates.

© 2025 Elanco or its affiliates

REVISED: November 2025

PA600574X

Principal Display Panel – 50 Tablets Bottle Label

Drontal™ Plus

(praziquantel/pyrantel pamoate/febantel) tablets

Broad spectrum anthelmintic for
puppies and small dogs (2 to 25 lbs.)

EACH TABLET CONTAINS: 22.7 mg praziquantel, 22.7 mg
pyrantel base as pyrantel pamoate, and 113.4 mg febantel.

CAUTION: Federal law restricts this drug to use by or on the
order of a licensed veterinarian.

WARNING: KEEP OUT OF REACH OF CHILDREN.

Elanco

50 Tablets

Manufactured for:
Elanco US Inc., Indianapolis, IN 46221 U.S.A.
Approved by FDA under NADA # 141-007

Principal Display Panel – 50 Tablets Bottle Label

Drontal™ Plus

(praziquantel/pyrantel pamoate/febantel) tablets

Broad spectrum anthelmintic for
medium sized dogs (26 to 60 lbs.)

EACH TABLET CONTAINS: 68.0 mg praziquantel,
68.0 mg pyrantel base as pyrantel pamoate, and
340.2 mg febantel.

CAUTION: Federal law restricts this drug to use by
or on the order of a licensed veterinarian.

WARNING: KEEP OUT OF REACH OF CHILDREN.

Elanco

50 Tablets

Manufactured for: Elanco US Inc.
Indianapolis, IN 46221 U.S.A
Approved by FDA under NADA # 141-007

Principal Display Panel – 30 Tablets Bottle Label

Drontal™ Plus

(praziquantel/pyrantel pamoate/febantel) tablets

Broad spectrum anthelmintic for
large dogs (45 lbs. and greater)

EACH TABLET CONTAINS: 136.0 mg praziquantel,
136.0 mg pyrantel base as pyrantel pamoate, and
680.4 mg febantel.

CAUTION: Federal law restricts this drug to use
by or on the order of a licensed veterinarian.

WARNING: KEEP OUT OF REACH OF CHILDREN.

Elanco

30 Tablets

Manufactured for:
Elanco US Inc.
Indianapolis, IN 46221 U.S.A.
Approved by FDA under NADA # 141-007